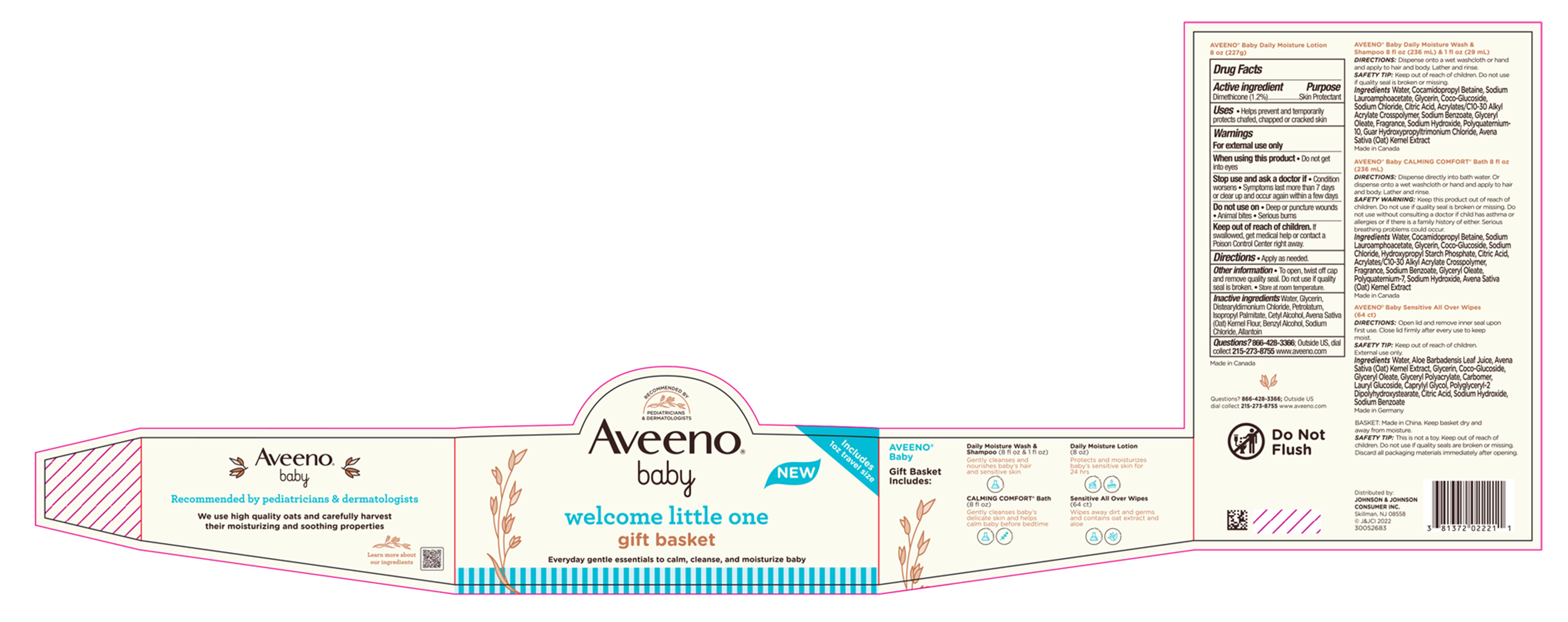 DRUG LABEL: Aveeno Baby Welcome Little One Gift Basket
NDC: 69968-0766 | Form: KIT | Route: TOPICAL
Manufacturer: Kenvue Brands LLC
Category: otc | Type: HUMAN OTC DRUG LABEL
Date: 20241106

ACTIVE INGREDIENTS: DIMETHICONE 12 mg/1 g
INACTIVE INGREDIENTS: PETROLATUM; OAT; BENZYL ALCOHOL; ALLANTOIN; DISTEARYLDIMONIUM CHLORIDE; CETYL ALCOHOL; SODIUM CHLORIDE; ISOPROPYL PALMITATE; WATER; GLYCERIN

Aveeno® Baby Welcome Little One Gift Basket

Aveeno® baby daily moisture lotion

Drug Facts

Active ingredient

Dimethicone 1.2%

Purpose

Skin Protectant

Uses

- Helps prevent and temporarily protects chafed, chapped or cracked skin

Warnings

For external use only

When using this product

- Do not get into eyes

Stop use and ask a doctor if

- Condition worsens
- Symptoms last more than 7 days or clear up and occur again within a few days

Do not use on

- Deep or puncture wounds
- Animal bites
- Serious burns

Keep out of reach of children. If swallowed, get medical help or contact a Poison Control Center right away.

Directions

- Apply as needed.

Other information

- To open, twist off cap and remove quality seal. Do not use if quality seal is broken.
- Store at room temperature.

Inactive ingredients

Water, Glycerin, Distearyldimonium Chloride, Petrolatum, Isopropyl Palmitate, Cetyl Alcohol, Avena Sativa (Oat) Kernel Flour, Benzyl Alcohol, Sodium Chloride, Allantoin

Questions?

866-428-3366; Outside US, dial collect 215-273-8755 www.aveeno.com

Distributed by:
JOHNSON & JOHNSON CONSUMER INC.
Skillman, NJ 08558

PRINCIPAL DISPLAY PANEL - Kit Package

RECOMMENDED BY

PEDIATRICIANS

& DERMATOLOGISTS

Aveeno®

baby

NEW

Includes

1oz travel size

welcome little one

gift basket

Everyday gentle essentials to calm, cleanse, and moisturize baby

Aveeno®

baby

Gift basket

Includes :

Daily Moisture Wash &

Shampoo (8 fl oz & 1 fl oz)

Gently cleanses and

nourishes baby’s hair

and sensitive skin

CALMING COMFORT® Bath

(8 fl oz)

Gently cleanses baby’s

delicate skin and helps

calm baby before bedtime

Daily Moisture Lotion

(8 fl oz)

Protects and moisturizes

baby’s sensitive skin for

24hrs

Sensitive All Over Wipes

(64 ct)

Wipes away dirt and germs

and contains oat extract and

aloe